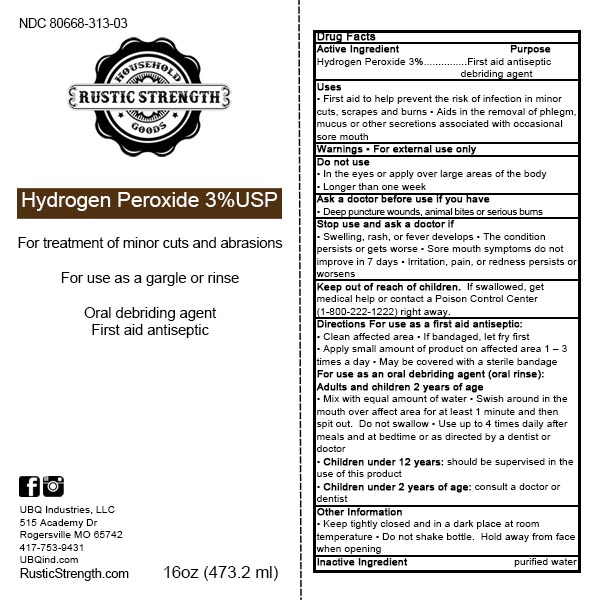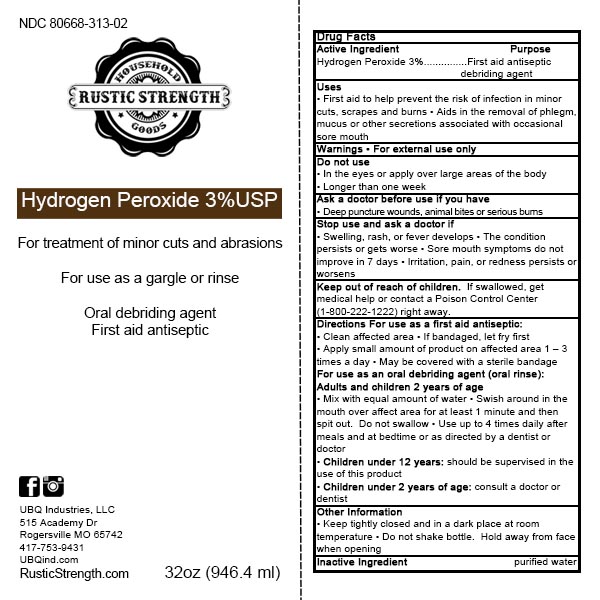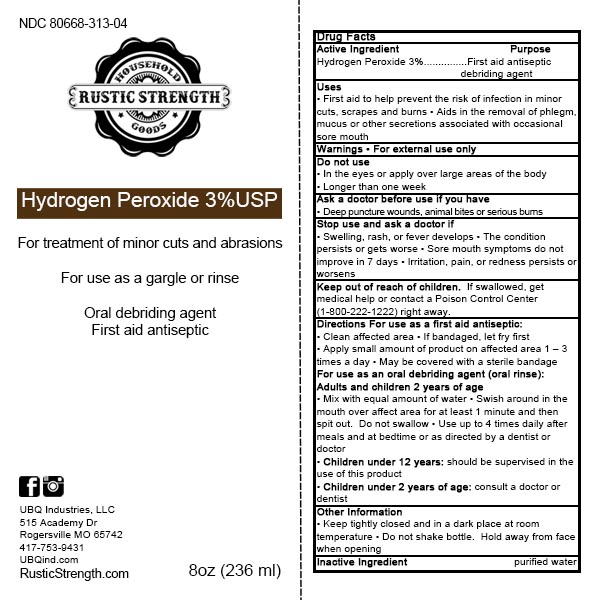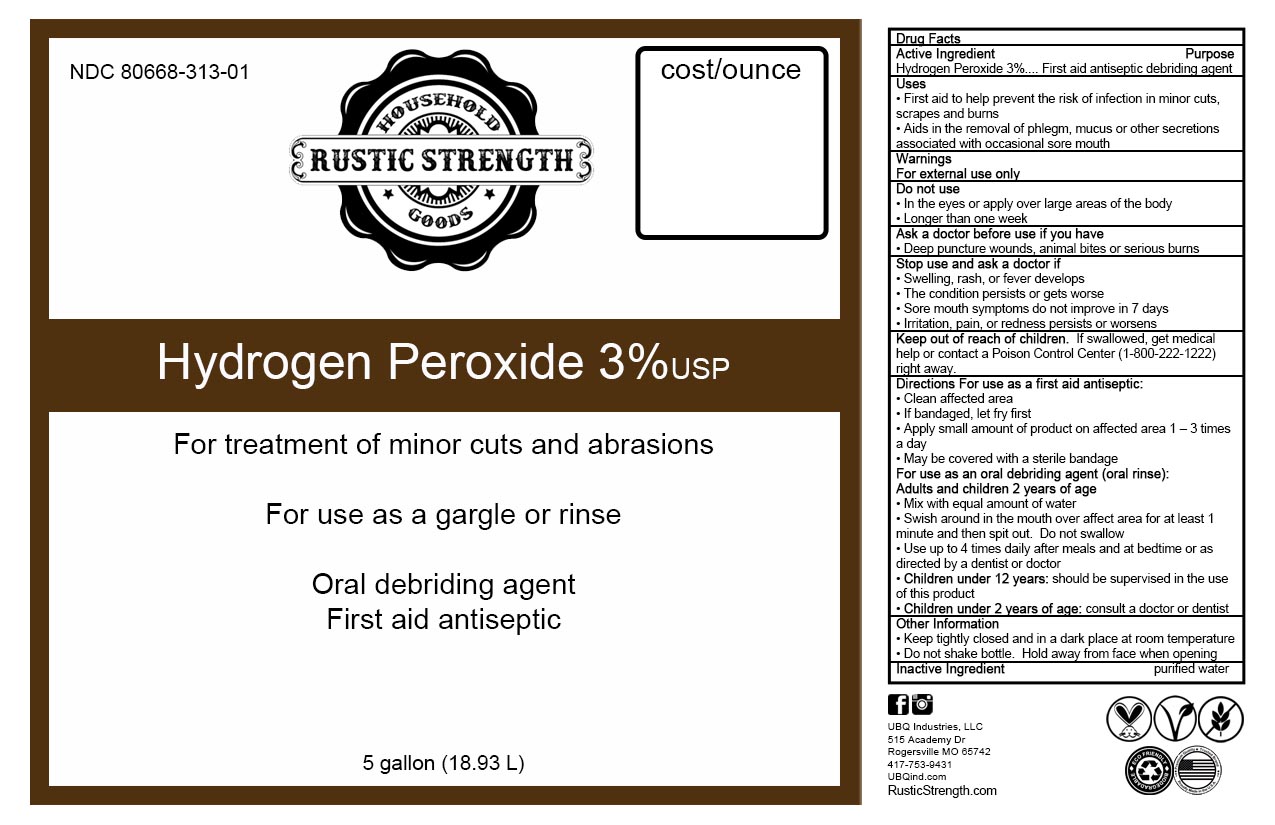 DRUG LABEL: Hydrogen Peroxide
NDC: 80668-313 | Form: LIQUID
Manufacturer: UBQ Industries, LLC
Category: otc | Type: HUMAN OTC DRUG LABEL
Date: 20211123

ACTIVE INGREDIENTS: HYDROGEN PEROXIDE 0.03 mL/100 mL
INACTIVE INGREDIENTS: WATER

Hydrogen Peroxide 3%

Hydrogen Peroxide 3% v/v First aid anitseptic debriding agent

First aid antiseptic debriding agent

Indications and usage section

• First aid to help prevent the risk of infection in minor cuts, scrapes and burns
• Aids in the removal of phlegm, mucus or other secretions associated with occasional sore mouth

Warnings Section

For external use only

Do not use

• In the eyes or apply over large areas of the body
• Longer than one week

Ask a doctor before use if you have

• Deep puncture wounds, animal bites or serious burns

Stop use and ask a doctor if

• Swelling, rash, or fever develops
• The condition persists or gets worse
• Sore mouth symptoms do not improve in 7 days
• Irritation, pain, or redness persists or worsens

Keep out of reach of children.

If swallowed, get medical help or contact a Poison Control Center (1-800-222-1222) right away.

Directions For use as a first aid antiseptic:

• Clean affected area
• If bandaged, let fry first
• Apply small amount of product on affected area 1 – 3 times a day
• May be covered with a sterile bandage
For use as an oral debriding agent (oral rinse):
Adults and children 2 years of age
• Mix with equal amount of water
• Swish around in the mouth over affect area for at least 1 minute and then spit out. Do not swallow
• Use up to 4 times daily after meals and at bedtime or as directed by a dentist or doctor
• Children under 12 years: should be supervised in the use of this product
• Children under 2 years of age: consult a doctor or dentist

Other Information

• Keep tightly closed and in a dark place at room temperature
• Do not shake bottle. Hold away from face when opening

Inactive Ingredients

Purified water

Package Label - Principal Display Panel

236 ml NDC 80668-313-04

473.2 ml NDC 80668-313-03

18927 ml NDC 80668-313-01

946.4 ml NDC 80668-313-02